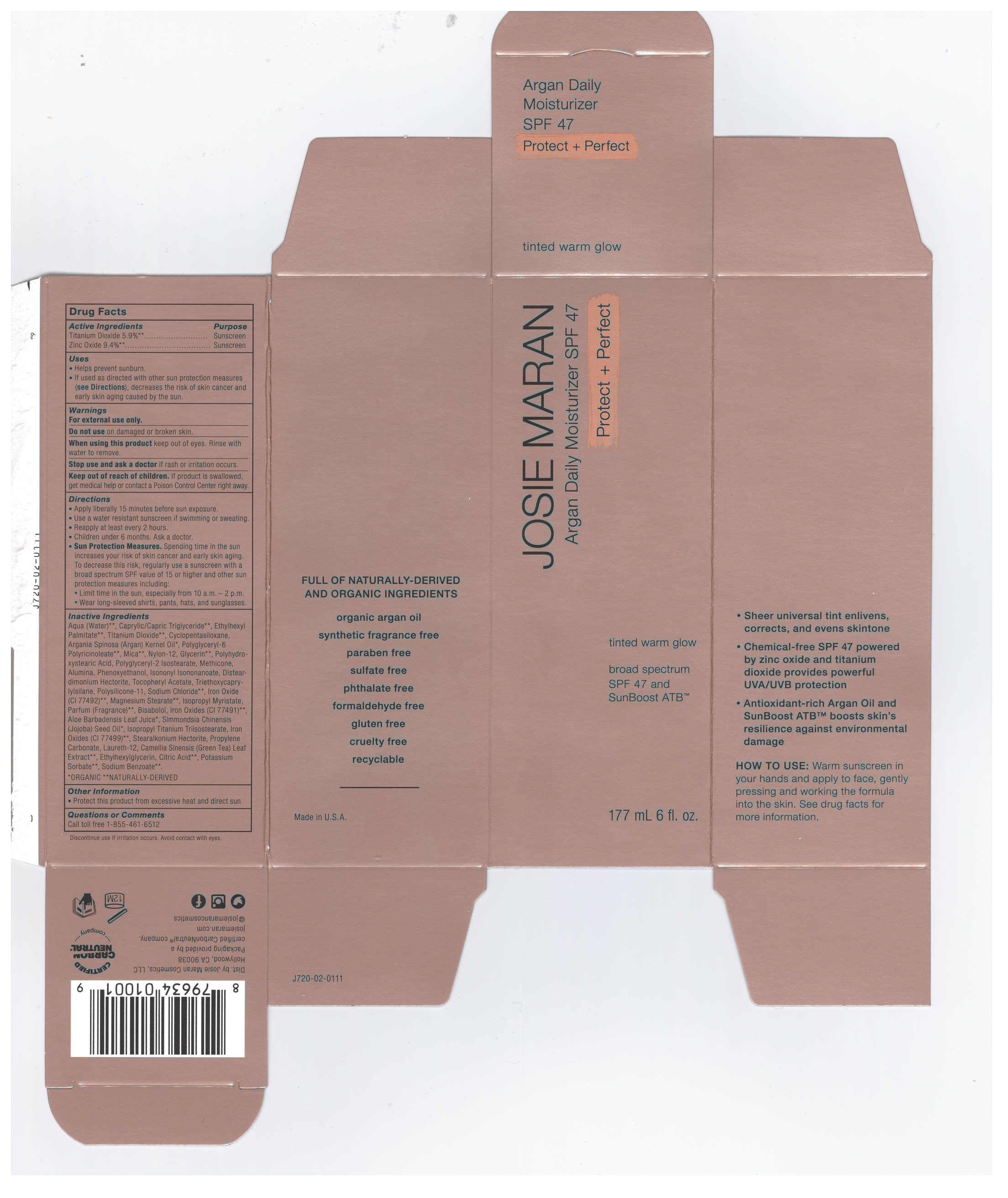 DRUG LABEL: Josie Maran Argan Daily Moisturizer SPF47 Protect and Perfect
NDC: 51514-0337 | Form: LOTION
Manufacturer: Autumn Harp, Inc.
Category: otc | Type: HUMAN OTC DRUG LABEL
Date: 20240102

ACTIVE INGREDIENTS: ZINC OXIDE 9.4 mg/100 mL; TITANIUM DIOXIDE 5.9 mg/100 mL
INACTIVE INGREDIENTS: WATER; MEDIUM-CHAIN TRIGLYCERIDES; ETHYLHEXYL PALMITATE; CYCLOMETHICONE 5; POLYGLYCERYL-6 DIOLEATE; MICA; ARGAN OIL; NYLON-12; GLYCERIN; POLYHYDROXYSTEARIC ACID (2300 MW); POLYGLYCERYL-2 MONOISOSTEARATE; METHICONE (20 CST); ALUMINUM OXIDE; PHENOXYETHANOL; ISONONYL ISONONANOATE; .ALPHA.-TOCOPHEROL ACETATE; DISTEARDIMONIUM HECTORITE; TRIETHOXYCAPRYLYLSILANE; POLYSILICONE-15; SODIUM CHLORIDE; FERRIC OXIDE YELLOW; MAGNESIUM STEARATE; ISOPROPYL MYRISTATE; APRICOT; LEVOMENOL; FERRIC OXIDE RED; JOJOBA OIL; ALOE VERA LEAF; ISOPROPYL TITANIUM TRIISOSTEARATE; FERROSOFERRIC OXIDE; STEARALKONIUM HECTORITE; LINALOOL, (+)-; PROPYLENE CARBONATE; LAURETH-12; LIMONENE, (+)-; GREEN TEA LEAF; .ALPHA.-AMYLCINNAMALDEHYDE; ETHYLHEXYLGLYCERIN; CITRIC ACID ACETATE; POTASSIUM SORBATE; SODIUM BENZOATE

Josie Maran Argan Daily Moisturizer SPF47 Protect and Perfect

Drug Facts

Active Ingredients

Zinc Oxide 9.4%**

Titanium Dioxide 5.9%**

Purpose

Sunscreen

Sunscreen

Uses

· Helps prevent sunburn

· If used as directed with other sun protection measures (see Directions), decreases the risk of skin cancer and early skin aging caused by the sun.

Warnings

For external use only

Do not use on damaged or broken skin.

Stop use and ask a doctor if rash occurs.

When using this product

· keep out of eyes

· Rinse with water to remove

Keep out of reach of children. If product is swallowed, get medical help or contact a Poison Control Center right away.

Directions:

• apply liberally 15 minutes before sun exposure

• use a water resistant sunscreen if swimming or sweating

• reapply at least every 2 hours

• children under 6 months: Ask a doctor

WHEN USING

Sun Protection Measures. Spending time in the sun increases your risk of skin cancer and early skin aging. To decrease the risk, regularly use a sunscreen with a Broad Spectrum SPF value of 15 or higher and other sun protection measures including:

• Limit time in the sun, especially from 10am - 2pm.

• Wear long-sleeve shirts, pants, hats, and sunglasses

Inactive Ingredients:

Aqua (Water)**, Caprylic/Capric Triglyceride**, Ethylhexyl Palmitate**, Titanium Dioxide**, Cyclopentasiloxane, Argania Spinosa (Argan) Kernel Oil**, Polyglyceryl-6 Polyricinoleate**, Mica**, Nylon-12, Glycerin**, Polyhydroxystearic Acid, Polyglyceryl-2 Isostearate, Methicone, Alumina, Phenoxyethanol, Isononyl Isononanoate, Disteardimonium Hectorite, Tocopheryl Acetate, Triethoxycaprylylsilane, Polysilicone-11, Sodium Chloride**, Iron Oxide (CI 77492)**, Magnesium Stearate**, Isopropyl Myristate, Fragrance**, Bisabolol, Iron Oxides (CI 77491)**, Aloe Barbadensis Leaf Juice*, Simmondsia Chinensis (Jojoba) Seed Oil*, Isopropyl Titanium Triisostearate, Iron Oxides (CI 77499)**, Stearalkonium Hectorite, Propylene Carbonate, Laureth-12, Camellia Sinensis (Green Tea) Leaf Extract**, Ethylhexylglycerin, Citric Acid**, Potassium Sorbate**, Sodium Benzoate**.

* Organic ** Natural

Other Information:

· Protect this product from excessive heat and direct sun.

DOSAGE AND ADMINISTRATION

Apply every two hours

Do not use on broken or damaged skin

Keep out of reach of children